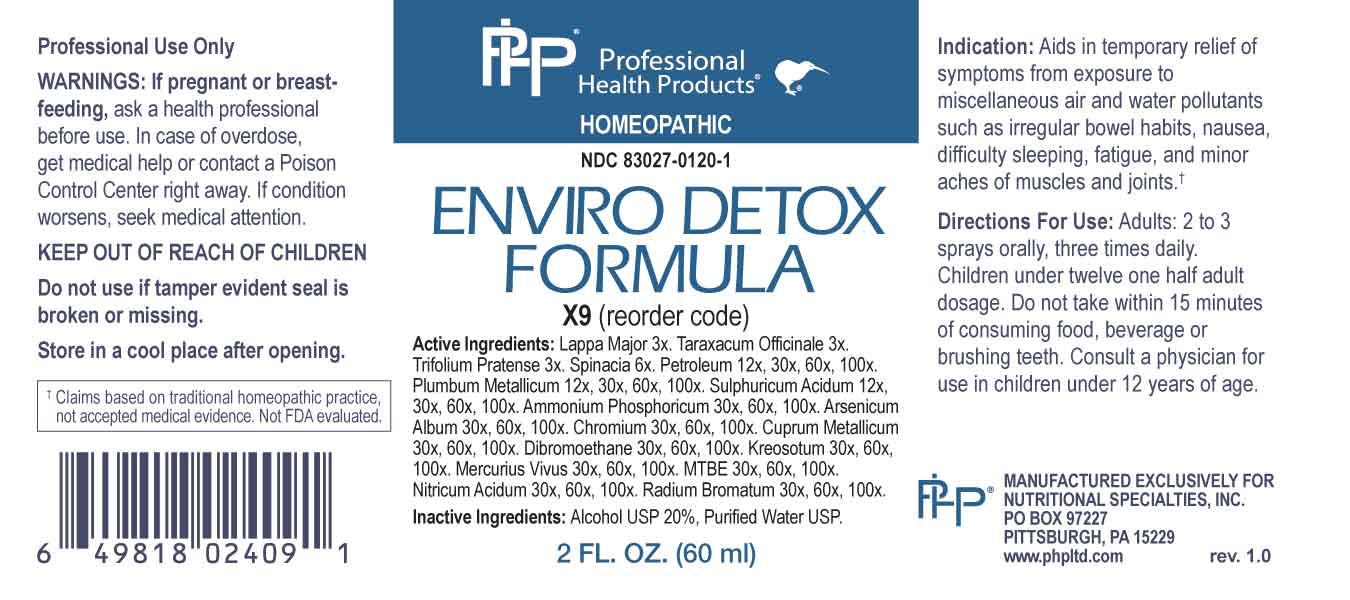 DRUG LABEL: Enviro Detox Formula
NDC: 83027-0120 | Form: SPRAY
Manufacturer: Nutritional Specialties, Inc.
Category: homeopathic | Type: HUMAN OTC DRUG LABEL
Date: 20231006

ACTIVE INGREDIENTS: ARCTIUM LAPPA ROOT 3 [hp_X]/1 mL; TARAXACUM OFFICINALE 3 [hp_X]/1 mL; TRIFOLIUM PRATENSE FLOWER 3 [hp_X]/1 mL; SPINACIA OLERACEA ROOT 6 [hp_X]/1 mL; KEROSENE 12 [hp_X]/1 mL; LEAD 12 [hp_X]/1 mL; SULFURIC ACID 12 [hp_X]/1 mL; AMMONIUM PHOSPHATE, DIBASIC 30 [hp_X]/1 mL; ARSENIC TRIOXIDE 30 [hp_X]/1 mL; CHROMIUM 30 [hp_X]/1 mL; COPPER 30 [hp_X]/1 mL; ETHYLENE DIBROMIDE 30 [hp_X]/1 mL; WOOD CREOSOTE 30 [hp_X]/1 mL; MERCURY 30 [hp_X]/1 mL; TERT-BUTYL METHYL ETHER 30 [hp_X]/1 mL; NITRIC ACID 30 [hp_X]/1 mL; RADIUM BROMIDE 30 [hp_X]/1 mL
INACTIVE INGREDIENTS: WATER; ALCOHOL

DRUG FACTS:

ACTIVE INGREDIENTS:

Lappa Major 3X, Taraxacum Officinale 3X, Trifolium Pratense 3X, Spinacia 6X, Petroleum 12X, 30X, 60X, 100X, Plumbum Metallicum 12X, 30X, 60X, 100X, Sulphuricum Acidum 12X, 30X, 60X, 100X, Ammonium Phosphoricum 30X, 60X, 100X, Arsenicum Album 30X, 60X, 100X, Chromium 30X, 60X, 100X, Cuprum Metallicum 30X, 60X, 100X, Dibromoethane 30X, 60X, 100X, Kreosotum 30X, 60X, 100X, Mercurius Vivus 30X, 60X, 100X, MTBE 30X, 60X, 100X, Nitricum Acidum 30X, 60X, 100X, Radium Bromatum 30X, 60X, 100X.

PURPOSE:

Aids in temporary relief of symptoms from exposure to miscellaneous air and water pollutants such as irregular bowel habits, nausea, difficulty sleeping, fatigue, and minor aches of muscles and joints.†

†Claims based on traditional homeopathic practice, not accepted medical evidence. Not FDA evaluated.

WARNINGS:

Professional Use Only

If pregnant or breast-feeding, ask a health professional before use.

In case of overdose, get medical help or contact a Poison Control Center right away.

If condition worsens, seek medical attention.

KEEP OUT OF REACH OF CHILDREN

Do not use if tamper evident seal is broken or missing.

Store in a cool place after opening

KEEP OUT OF REACH OF CHILDREN:

In case of overdose, get medical help or contact a Poison Control Center right away.

DIRECTIONS:

Adults: 2 to 3 sprays orally, three times daily. Children under twelve one half adult dosage. Do not take within 15 minutes of consuming food, beverage or brushing teeth. Consult a physician for use in children under 12 years of age.

INDICATIONS:

Aids in temporary relief of symptoms from exposure to miscellaneous air and water pollutants such as irregular bowel habits, nausea, difficulty sleeping, fatigue, and minor aches of muscles and joints.†

†Claims based on traditional homeopathic practice, not accepted medical evidence. Not FDA evaluated.

INACTIVE INGREDIENTS:

Alcohol USP 20%, Purified Water USP.

QUESTIONS:

MANUFACTURED EXCLUSIVELY FOR

NUTRITIONAL SPECIALTIES, INC.

PO BOX 97227

PITTSBURG, PA 15229

www.phpltd.com

PACKAGE LABEL DISPLAY:

Professional

Health Products

HOMEOPATHIC

NDC 83027-0120-1

ENVIRO DETOX

FORMULA

2 FL. OZ (60 ml)